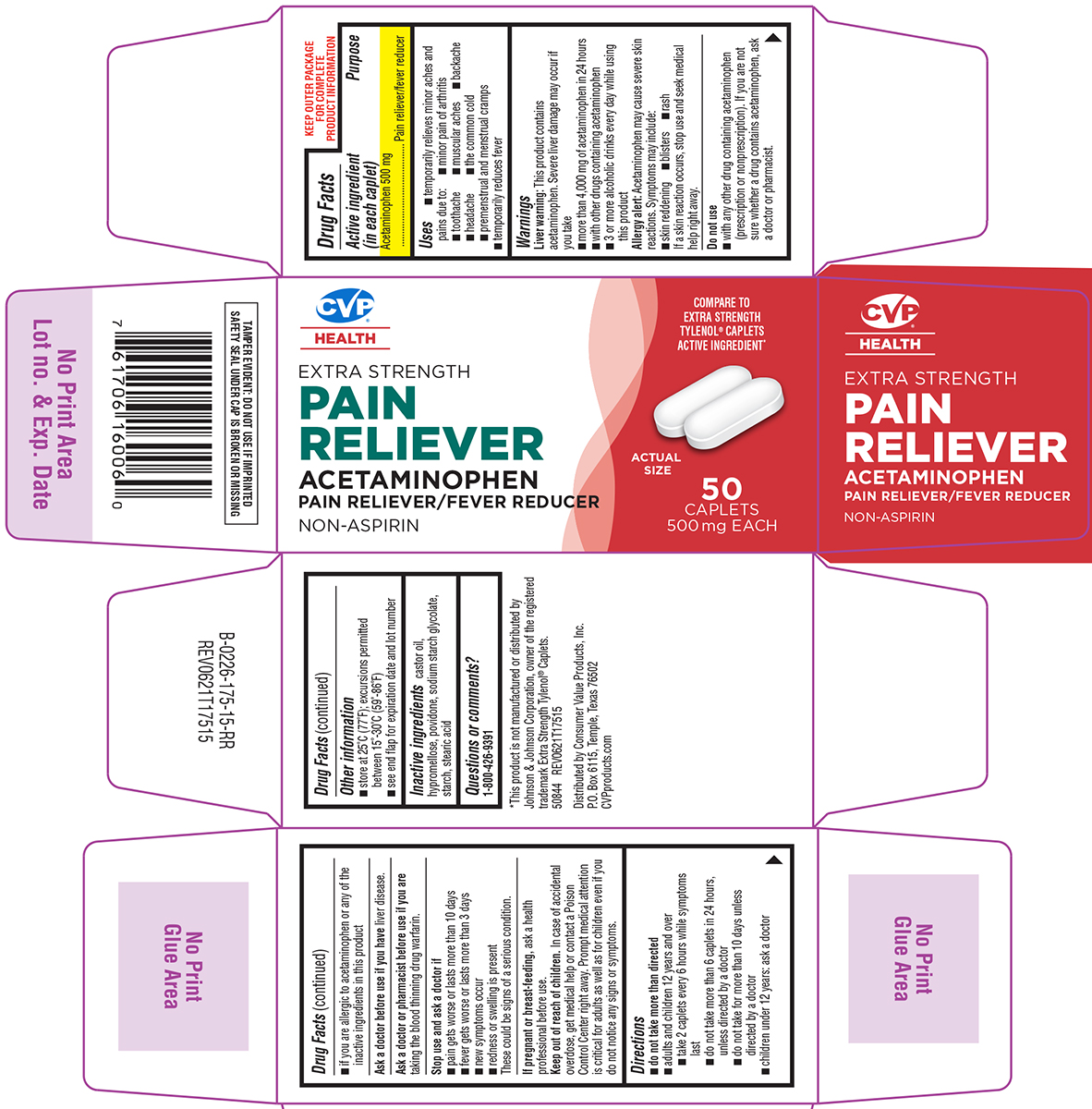 DRUG LABEL: Pain Reliever
NDC: 57243-175 | Form: TABLET, FILM COATED
Manufacturer: Salado Sales, Inc.
Category: otc | Type: HUMAN OTC DRUG LABEL
Date: 20250416

ACTIVE INGREDIENTS: ACETAMINOPHEN 500 mg/1 1
INACTIVE INGREDIENTS: CASTOR OIL; HYPROMELLOSE, UNSPECIFIED; POVIDONE, UNSPECIFIED; SODIUM STARCH GLYCOLATE TYPE A POTATO; STARCH, CORN; STEARIC ACID

Pain Reliever

Active ingredient (in each caplet)

Acetaminophen 500 mg

Purpose

Pain reliever/fever reducer

Uses

- temporarily relieves minor aches and pains due to:
  - minor pain of arthritis
  - toothache
  - muscular aches
  - backache
  - headache
  - the common cold
  - premenstrual and menstrual cramps
- temporarily reduces fever

Warnings

Liver warning: This product contains acetaminophen. Severe liver damage may occur if you take

- more than 4,000 mg of acetaminophen in 24 hours
- with other drugs containing acetaminophen
- 3 or more alcoholic drinks every day while using this product

Allergy alert: Acetaminophen may cause severe skin reactions. Symptoms may include:

- skin reddening
- blisters
- rash

If a skin reaction occurs, stop use and seek medical help right away.

Do not use

- with any other drug containing acetaminophen (prescription or nonprescription). If you are not sure whether a drug contains acetaminophen, ask a doctor or pharmacist.
- if you are allergic to acetaminophen or any of the inactive ingredients in this product

Ask a doctor before use if you have

liver disease.

Ask a doctor or pharmacist before use if you are

taking the blood thinning drug warfarin.

Stop use and ask a doctor if

- pain gets worse or lasts more than 10 days
- fever gets worse or lasts more than 3 days
- new symptoms occur
- redness or swelling is present

These could be signs of a serious condition.

If pregnant or breast-feeding,

ask a health professional before use.

Keep out of reach of children.

In case of accidental overdose, get medical help or contact a Poison Control Center right away. Prompt medical attention is critical for adults as well as for children even if you do not notice any signs or symptoms.

Directions

- do not take more than directed
- adults and children 12 years and over
  - take 2 caplets every 6 hours while symptoms last
  - do not take more than 6 caplets in 24 hours, unless directed by a doctor
  - do not take for more than 10 days unless directed by a doctor
- children under 12 years: ask a doctor

Other information

- store at 25°C (77°F); excursions permitted between 15°-30°C (59°-86°F)
- see end flap for expiration date and lot number

Inactive ingredients

castor oil, hypromellose, povidone, sodium starch glycolate, starch, stearic acid

Questions or comments?

1-800-426-9391

Principal Display Panel

CVP®
HEALTH

COMPARE TO
EXTRA STRENGTH
TYLENOL® CAPLETS
ACTIVE INGREDIENT*

EXTRA STRENGTH
PAIN
RELIEVER

ACETAMINOPHEN
PAIN RELIEVER/FEVER REDUCER

NON-ASPIRIN

ACTUAL
SIZE

50
CAPLETS
500 mg EACH

TAMPER EVIDENT: DO NOT USE IF IMPRINTED
SAFETY SEAL UNDER CAP IS BROKEN OR MISSING

*This product is not manufactured or distributed by
Johnson & Johnson Corporation, owner of the registered
trademark Extra Strength Tylenol® Caplets.

50844 REV0621T17515

Distributed by Consumer Value Products, Inc.
P.O. Box 6115, Temple, Texas 76502
CVPproducts.com

CVP 44-175